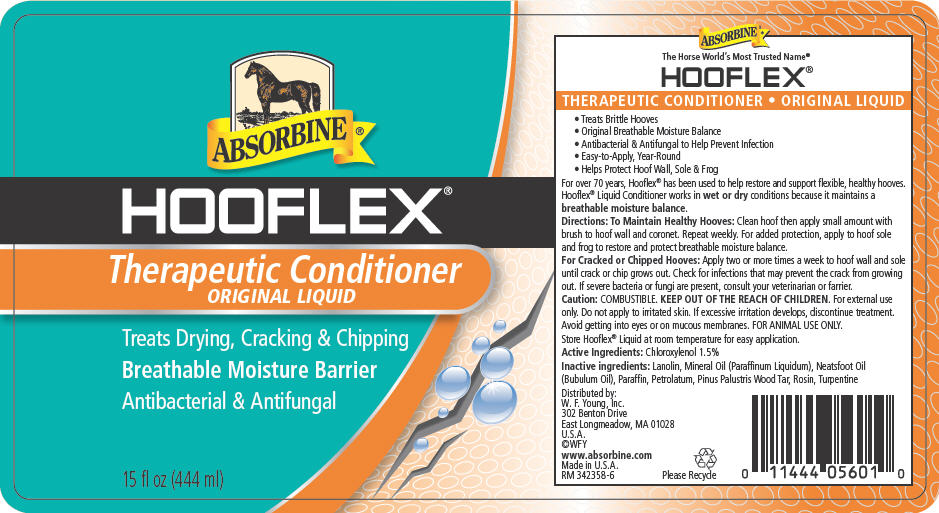 DRUG LABEL: Absorbine Hooflex 
NDC: 11444-056 | Form: LIQUID
Manufacturer: W. F. Young, Inc.
Category: animal | Type: OTC ANIMAL DRUG LABEL
Date: 20160623

ACTIVE INGREDIENTS: CHLOROXYLENOL 1.5 g/100 mL
INACTIVE INGREDIENTS: LANOLIN; NEATSFOOT OIL

ABSORBINE® HOOFLEX® Therapeutic Conditioner ORIGINAL LIQUID

VETERINARY INDICATIONS

- Treats Brittle Hooves
- Original Breathable Moisture Balance
- Antibacterial & Antifungal to Help Prevent Infection
- Easy-to-Apply, Year-Round
- Helps Protect Hoof Wall, Sole & Frog

DESCRIPTION

For over 70 years, Hooflex® has been used to help restore and support flexible, healthy hooves. Hooflex® Liquid Conditioner works in wet or dry conditions because it maintains a breathable moisture balance.

Directions

To Maintain Healthy Hooves

Clean hoof then apply small amount with brush to hoof wall and coronet. Repeat weekly. For added protection, apply to hoof sole and frog to restore and protect breathable moisture balance.

For Cracked or Chipped Hooves

Apply two or more times a week to hoof wall and sole until crack or chip grows out. Check for infections that may prevent the crack from growing out. If severe bacteria or fungi are present, consult your veterinarian or farrier.

Caution

COMBUSTIBLE.

KEEP OUT OF THE REACH OF CHILDREN.

WHEN USING

For external use only.

Do not apply to irritated skin.

STOP USE

If excessive irritation develops, discontinue treatment.

WHEN USING

Avoid getting into eyes or on mucous membranes. FOR ANIMAL USE ONLY.

STORAGE AND HANDLING

Store Hooflex® Liquid at room temperature for easy application.

Active Ingredients

Chloroxylenol 1.5%

Inactive ingredients

Lanolin, Mineral Oil (Paraffinum Liquidum), Neatsfoot Oil (Bubulum Oil), Paraffin, Petrolatum, Pinus Palustris Wood Tar, Rosin, Turpentine

Distributed by:
W. F. Young, Inc.
302 Benton Drive
East Longmeadow, MA 01028
U.S.A.

PRINCIPAL DISPLAY PANEL- 444 ml Bottle Label

ABSORBINE ®

HOOFLEX®
Therapeutic Conditioner
ORIGINAL LIQUID

Treats Drying, Cracking & Chipping
Breathable Moisture Barrier
Antibacterial & Antifungal

15 fl oz (444 ml)